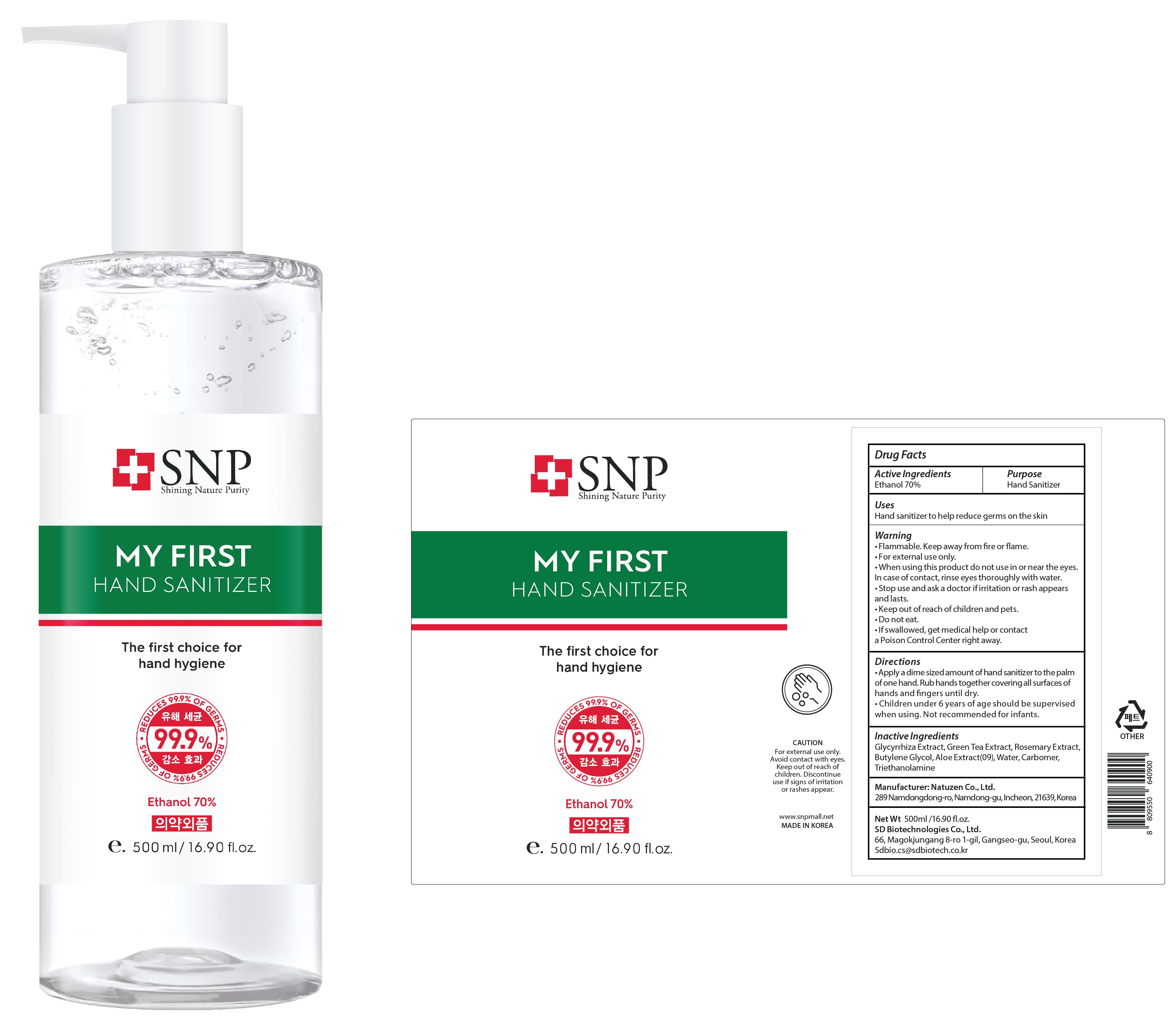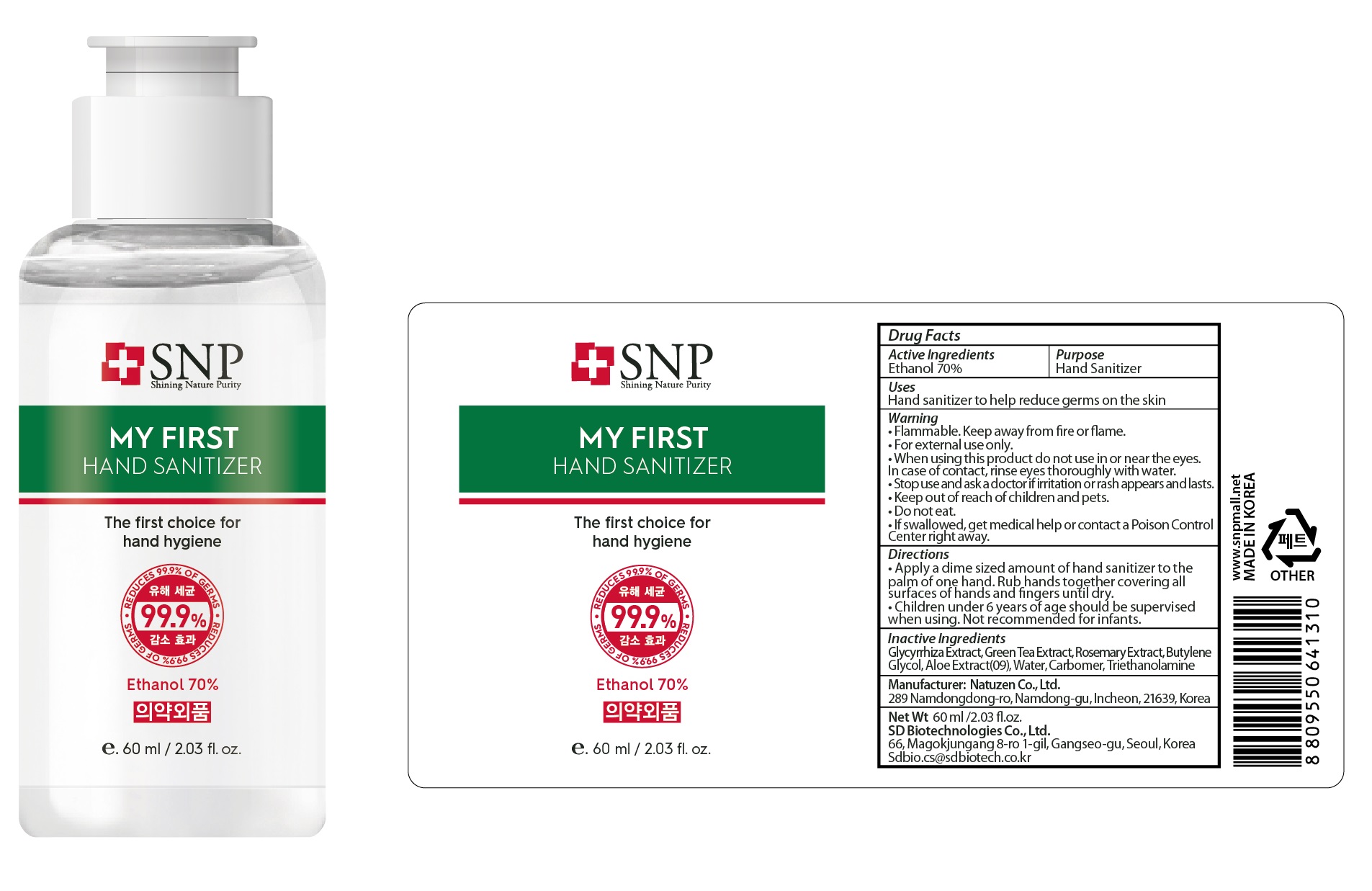 DRUG LABEL: SNP MY FIRST HAND SANITIZER
NDC: 70142-112 | Form: GEL
Manufacturer: SD BIOTECHNOLOGIES CO., LTD
Category: otc | Type: HUMAN OTC DRUG LABEL
Date: 20200401

ACTIVE INGREDIENTS: ALCOHOL 350 g/100 mL
INACTIVE INGREDIENTS: Water; LICORICE; GREEN TEA LEAF; Butylene Glycol; CARBOMER HOMOPOLYMER, UNSPECIFIED TYPE; TROLAMINE

ACTIVE INGREDIENT

Active ingredients: Ethanol 70%

PURPOSE

Purpose: Hand Sanitizer

WARNINGS

• Flammable. Keep away from fire or flame.
• For external use only.
• When using this product do not use in or near the eyes.
In case of contact, rinse eyes thoroughly with water.
• Stop use and ask a doctor if irritation or rash appears
and lasts.
• Keep out of reach of children and pets.
• Do not eat.
• If swallowed, get medical help or contact a Poison Control Center right away.

KEEP OUT OF REACH OF CHILDREN

Uses

Hand sanitizer to help reduce germs on the skin

Directions

• Apply a dime sized amount of hand sanitizer to the palm of one hand. Rub hands together covering all surfaces of hands and fingers until dry.
• Children under 6 years of age should be supervised when using. Not recommended for infants.

INACTIVE INGREDIENT

Inactive ingredients:

Glycyrrhiza Extract, Green Tea Extract, Rosemary Extract, Butylene Glycol, Aloe Extract(09), Water, Carbomer, Triethanolamine